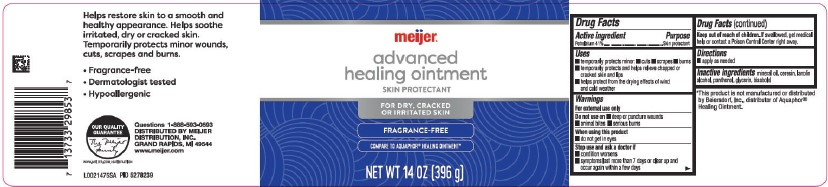 DRUG LABEL: Healing
NDC: 41250-059 | Form: OINTMENT
Manufacturer: Meijer, Inc.
Category: otc | Type: HUMAN OTC DRUG LABEL
Date: 20260219

ACTIVE INGREDIENTS: PETROLATUM 410 mg/1 g
INACTIVE INGREDIENTS: MINERAL OIL; CERESIN; LANOLIN ALCOHOLS; PANTHENOL; GLYCERIN; LEVOMENOL

Meijer 247.000/247AA-AC
Healing Ointment for Dry and Cracked Skin

Active ingredient

Petrolatum 41%

Purpose

Skin protectant

Uses

- temporarily protects minor: cuts, scrapes, burns
- temporarily protects and helps relieve chapped or cracked skin and lips
- helps protect from the drying effects of wind and cold weather

Warnings

For external use only

Do not use on

- deep or puncture wounds
- animal bites
- serious burns

When using this product

- do not get into eyes

Stop use and ask a doctor if

- condition worsens
- symptoms last more than 7 days or clear up and occur again with in a few days

Keep out of reach of children

If swallowed, get medical help or contact a Poison Control Center right away.

Directions

- apply as needed

Inactive ingredients

mineral oil, ceresin, lanolin alcohol, panthenol, glycerin, bisabolol

Disclaimer

*This product is not manufactured or distributed by Beiersdorf AG, distributor of Aquaphor® Healing Ointment.

Claims

Helps restore skin to a smooth and healthy appearance. Helps soothe irritated, dry or cracked skin.

Temporarily protects minor wounds, cuts, scrapes and burns.

- Fragrance-free
- Dermatologist tested
- Hypoallergenic

Adverse Reactions

Questions 1-888-593-0593

DISTRIBUTED BY

MEIJER DISTRIBUTION, INC.

GRAND RAPIDS, MI 49544

www.meijer.com

OUR QUALITY GUARANTEE

The Meijer Family

www.meijer.com/satisfaction

Principal display panel

meijer®

ADVANCED healing Ointment

SKIN PROTECTANT

FOR DRY, CRACKED OR IRRITATED SKIN

FRAGRANCE-FREE

COMPARE TO AQUAPHOR®HEALING OINTMENT*

NET WT 14 OZ (396 g)